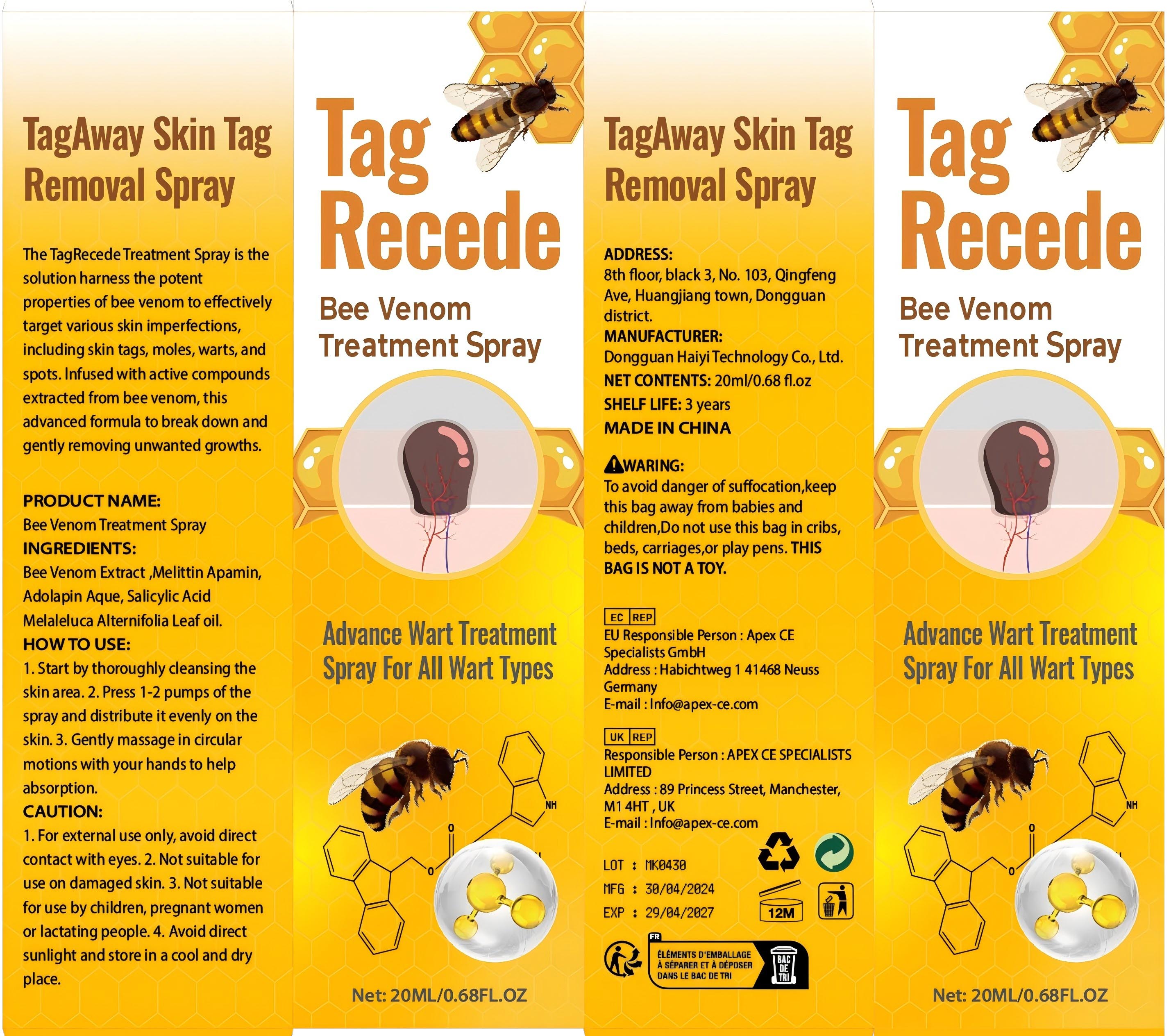 DRUG LABEL: Bee Venom Treatment
NDC: 84732-064 | Form: SPRAY
Manufacturer: Dongguan Haiyi Technology Co.,Ltd.
Category: otc | Type: HUMAN OTC DRUG LABEL
Date: 20241024

ACTIVE INGREDIENTS: APIS MELLIFERA VENOM 1 mg/20 mL
INACTIVE INGREDIENTS: MELITTIN; SALICYLIC ACID; TEA TREE OIL

Active ingredient

Bee Venom Extract

Inactive ingredient

Melittin Apamin,Adolapin Aque, Salicylic Acid，Melaleluca Alternifolia Leaf oil.

Purpose section

The TagRecedeTreatment Spray is thesolution harness the potentproperties of bee venom to effectivelytarget various skin imperfections,including skin tags, moles, warts, andspots.infused with active compoundsextracted from bee venom, thisadvanced formula to break down andgently removing unwanted growths.

Warning

To avoid danger of suffocation,keepthis bag away from babies andchildren,Do not use this bag in cribs,beds, carriages,or play pens. THlS BAG IS NOT A TOY.

stop use

This product may cause allergic reactions in asmall number of people.
lf youexperience any discomfort,please stop using it immediately.

not use

Not suitable for use by children, pregnantor breast feeding people.

OUT OF CHILDREN

KEEP THE PRODUCT OUT OF REACH OF CHILDREN to

HOW TO USE

1. Start by thoroughly cleansing theskin area.

2. Press 1-2 pumps of thespray and distribute it evenly on theskin.

3. Gently massage in circularmotions with your hands to helpabsorption.

Dosage

take an appropriateamount,Use 2-3 times a week